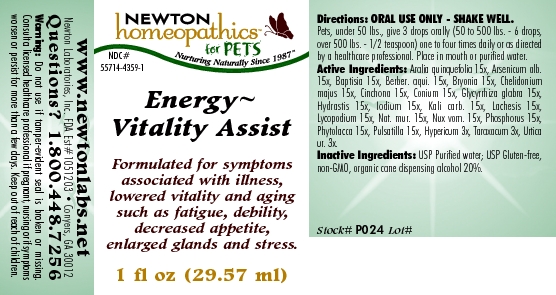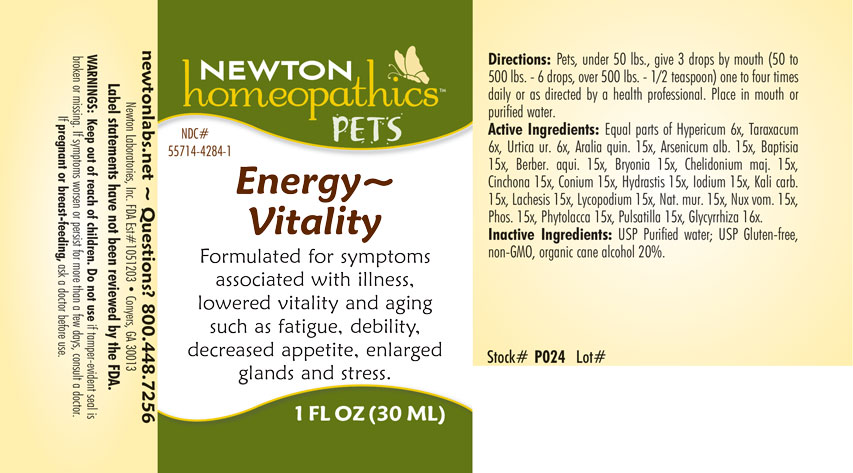 DRUG LABEL: Energy Vitality Assist
NDC: 55714-4359 | Form: LIQUID
Manufacturer: Newton Laboratories, Inc.
Category: homeopathic | Type: OTC ANIMAL DRUG LABEL
Date: 20190114

ACTIVE INGREDIENTS: American Ginseng 15 [hp_X]/1 mL; Arsenic Trioxide 15 [hp_X]/1 mL; Baptisia Tinctoria 15 [hp_X]/1 mL; Mahonia Aquifolium Root Bark 15 [hp_X]/1 mL; Bryonia Alba Root 15 [hp_X]/1 mL; Chelidonium Majus 15 [hp_X]/1 mL; Cinchona Officinalis Bark 15 [hp_X]/1 mL; Conium Maculatum Flowering Top 15 [hp_X]/1 mL; Glycyrrhiza Glabra 15 [hp_X]/1 mL; Goldenseal 15 [hp_X]/1 mL; Iodine 15 [hp_X]/1 mL; Potassium Carbonate 15 [hp_X]/1 mL; Lachesis Muta Venom 15 [hp_X]/1 mL; Lycopodium Clavatum Spore 15 [hp_X]/1 mL; Sodium Chloride 15 [hp_X]/1 mL; Strychnos Nux-vomica Seed 15 [hp_X]/1 mL; Phosphorus 15 [hp_X]/1 mL; Phytolacca Americana Root 15 [hp_X]/1 mL; Pulsatilla Vulgaris 15 [hp_X]/1 mL; Hypericum Perforatum 3 [hp_X]/1 mL; Taraxacum Officinale 3 [hp_X]/1 mL; Urtica Urens 3 [hp_X]/1 mL
INACTIVE INGREDIENTS: Alcohol

Energy-Vitality

INDICATIONS & USAGE SECTION

Formulated for symptoms associated with illness, lowered vitality and aging such as fatigue, debility, decreased appetite, enlarged glands and stress.

DOSAGE & ADMINISTRATION SECTION

Directions: Pets, under 50 lbs., give 3 drops by mouth (50 to 500 lbs. - 6 drops, over 500 lbs. - 1/2 teaspoon) one to four times daily or as directed by a health professional. Place in mouth or purified water

OTC - ACTIVE INGREDIENT SECTION

Equal parts of Hypericum 6x, Taraxacum 6x, Urtica ur. 6x, Aralia quin. 15x, Arsenicum alb.15x, Baptisia 15x, Berber. aqui. 15x, Bryonia 15x, Chelidonium maj. 15x, Cinchona 15x, Conium 15x, Hydrastis 15x, Iodium 15x, Kali carb. 15x, Lachesis 15x, Lycopodium 15x, Nat. mur. 15x, Nux vom. 15x, Phos. 15x, Phytolacca 15x, Pulsatilla 15x, Glycyrrhiza 16x.

OTC - PURPOSE SECTION

Formulated for symptoms associated with illness, lowered vitality and aging such as fatigue, debility, decreased appetite, enlarged glands and stress.

INACTIVE INGREDIENT SECTION

USP Purified Water; USP Gluten-free, non-GMO, organic cane alcohol 20%.

QUESTIONS SECTION

newtonlabs.net - Questions? 800.448.7256 Newton Laboratories, Inc. FDA Est # 1051203 - Conyers, GA 30013

WARNINGS SECTION

WARNINGS: Keep out of reach of children. Do not use if tamper-evident seal is broken or missing. If symptoms worsen or persist for more than a few days, consult a doctor. If pregnant or breast-feeding, ask a doctor before use.

OTC - PREGNANCY OR BREAST FEEDING SECTION

If pregnant or breast-feeding, ask a doctor before use..

OTC - KEEP OUT OF REACH OF CHILDREN SECTION

Keep out of reach of children.